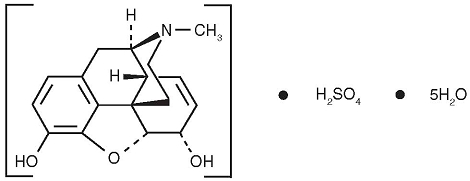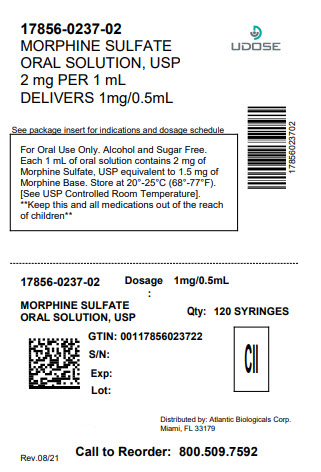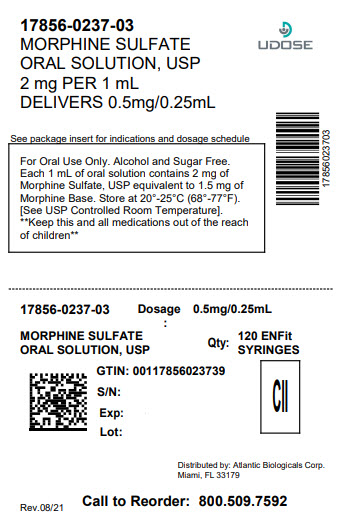 DRUG LABEL: Morphine Sulfate
NDC: 17856-0237 | Form: SOLUTION
Manufacturer: ATLANTIC BIOLOGICALS CORP.
Category: prescription | Type: HUMAN PRESCRIPTION DRUG LABEL
Date: 20240520
DEA Schedule: CII

ACTIVE INGREDIENTS: MORPHINE SULFATE 10 mg/5 mL
INACTIVE INGREDIENTS: CITRIC ACID MONOHYDRATE; EDETATE DISODIUM; FD&C GREEN NO. 3; GLYCERIN; SODIUM BENZOATE; SORBITOL; WATER

HIGHLIGHTS OF PRESCRIBING INFORMATION

These highlights do not include all the information needed to use Morphine Sulfate Oral Solution safely and effectively. See full prescribing information for Morphine Sulfate Oral Solution. Morphine Sulfate Oral Solution, CII Initial U.S. Approval: 1941

WARNING: RISK OF MEDICATION ERRORS

See full prescribing information for complete boxed warning

Morphine Sulfate Oral Solution is available in 10 mg per 5 mL, 20 mg per 5 mL and 100 mg per 5 mL (20 mg/mL) concentrations. The 100 mg per 5 mL (20 mg/mL) concentration is indicated for use in opioid-tolerant patients only.

Take care to avoid dosing errors due to confusion between different concentration and between mg and mL, which could result in accidental overdose and death. (5.1)

Keep Morphine Sulfate Oral Solution out of the reach of children.

1 INDICATIONS AND USAGE

Morphine sulfate is an opioid analgesic indicated for the relief of moderate to severe acute and chronic pain where an opioid analgesic is appropriate. () 1

Morphine sulfate 100 mg per 5 mL (20 mg/mL) solution is indicated for the relief of moderate to severe acute and chronic pain in opioid-tolerant patients. () 1

2 DOSAGE AND ADMINISTRATION

- Morphine Sulfate Oral Solution: 10 to 20 mg every 4 hours as needed. () 2.2

3 DOSAGE FORMS AND STRENGTHS

Oral Solution: For the 10 mg per 5 mL or 20 mg per 5 mL strengths, each mL contains 2 mg or 4 mg of morphine sulfate USP. For the 100 mg per 5 mL (20 mg/mL) strength, each mL contains 20 mg of morphine sulfate USP. () 3

4 CONTRAINDICATIONS

- Known hypersensitivity to morphine. () 4
- Respiratory depression in the absence of resuscitative equipment. () 4
- Acute or severe bronchial asthma or hypercarbia. () 4
- Paralytic ileus. () 4

5 WARNINGS AND PRECAUTIONS

- Risk of Medication Errors: Use caution when prescribing, dispensing, and administering to avoid dosing errors due to confusion between different concentrations and between mg and mL, which could result in accidental overdose and death. () 5.1
- Respiratory depression: Increased risk in elderly, debilitated patients, those suffering from conditions accompanied by hypoxia, hypercapnia, or upper airway obstruction. () 5.2
- Controlled substance: Morphine sulfate is a Schedule II controlled substance with an abuse liability similar to other opioids. () 5.3
- CNS effects: Additive CNS depressive effects when used in conjunction with alcohol, other opioids, or illicit drugs. () 5.4
- Elevation of intracranial pressure: May be markedly exaggerated in the presence of head injury, other intracranial lesions. () 5.5
- Hypotensive effect: Increased risk with compromised ability to maintain blood pressure. () 5.6
- Prolonged gastric obstruction: In patients with gastrointestinal obstruction, especially paralytic ileus. () 5.7
- Sphincter of Oddi spasm and diminished biliary/pancreatic secretions. Increased risk with biliary tract disease. () 5.8
- Special Risk Groups: Use with caution and in reduced dosages in patients with severe renal or hepatic impairment, Addison’s disease, hypothyroidism, prostatic hypertrophy, or urethral stricture, elderly, CNS depression, toxic psychosis, acute alcoholism and delirium tremens, may aggravate or induce seizures. () 5.9
- Impaired mental/physical abilities: Caution must be used with potentially hazardous activities. () 5.10

6 ADVERSE REACTIONS

Most common adverse reactions are constipation, nausea, somnolence, lightheadedness, dizziness, sedation, vomiting, sweating. () 6

To report SUSPECTED ADVERSE REACTIONS, contact Roxane Laboratories, Inc. at (614) 276-4000 or Technical Product Information (800) 962-8364 or FDA at 1-800-FDA-1088 or www.fda.gov/medwatch

7 DRUG INTERACTIONS

- CNS depressants: Increased risk of respiratory depression, hypotension, profound sedation, or coma. Use with caution in reduced dosages. () 7.1
- Muscle relaxants: Enhance the neuromuscular blocking action of skeletal muscle relaxants and produce an increased degree of respiratory depression. () 7.2
- Mixed agonist/antagonist opioid analgesics (i.e. pentazocine, nalbuphine, and butorphanol): May reduce the analgesic effect and/or may precipitate withdrawal symptoms. () 7.3
- Cimetidine: Precipitates apnea, confusion and muscle twitching. () 7.4
- Monoamine oxidase inhibitors (MAOIs): Potentiate the action of morphine sulfate. Morphine sulfate should not be used in patients taking MAOIs or within 14 days of stopping such treatment. () 7.5

8 USE IN SPECIFIC POPULATIONS

- Based on animal data, may cause fetal harm. (8.1)
- Geriatric patients (), Hepatic impairment (8.8), Renal impairment (): Use caution during dose selection, starting at the low end of the dosing range while carefully monitoring for side effects. 8.58.9

FULL PRESCRIBING INFORMATION

WARNING: RISK OF MEDICATION ERRORS

Morphine Sulfate Oral Solution is available in 10 mg per 5 mL, 20 mg per 5 mL and 100 mg per 5 mL (20 mg/mL) concentrations.

The 100 mg per 5 mL (20 mg/mL) concentration is indicated for use in opioid-tolerant patients only.

Take care when prescribing and administering Morphine Sulfate Oral Solution to avoid dosing errors due to confusion between different concentrations and between mg and mL, which could result in accidental overdose and death. Take care to ensure the proper dose is communicated and dispensed.

Keep Morphine Sulfate Oral Solution out of the reach of children. In case of accidental ingestion, seek emergency medical help immediately.

1 INDICATIONS AND USAGE

Morphine sulfate solution are formulations of morphine, an opioid agonist, indicated for the relief of moderate to severe acute and chronic pain where use of an opioid analgesic is appropriate. Morphine sulfate solution is an opioid analgesic indicated for the relief of moderate to severe acute and chronic pain in opioid-tolerant patients. oral (10 mg per 5 mL and 20 mg per 5 mL) oral 100 mg per 5 mL (20 mg/mL)

Morphine sulfate oral solution 100 mg per 5 mL (20 mg/mL) may cause fatal respiratory depression when administered to patients not previously exposed to opioids. Patients considered to be opioid tolerant are those who are taking at least 60 mg oral morphine per day, or at least 30 mg of oral oxycodone per day, or at least 12 mg hydromorphone per day, or an equianalgesic dose of another opioid, for a week or longer.

2 DOSAGE AND ADMINISTRATION

Morphine Sulfate Oral Solution is available in three concentrations: 10 mg per 5 mL, 20 mg per 5 mL and 100 mg per 5 mL (20 mg/mL).

Take care when prescribing and administering Morphine Sulfate Oral Solution to avoid dosing errors due to confusion between different concentrations and between mg and mL, which could result in accidental overdose and death. Take care to ensure the proper dose is communicated and dispensed. When writing prescriptions, include both the total dose in mg and the total dose in volume. Always use the enclosed calibrated oral syringe when administering Morphine Sulfate Oral Solution 100 mg per 5 mL (20 mg/mL) to ensure the dose is measured and administered accurately.

Selection of patients for treatment with morphine sulfate should be governed by the same principles that apply to the use of similar opioid analgesics. Individualize treatment in every case, using non-opioid analgesics, opioids on an as needed basis and/or combination products, and chronic opioid therapy in a progressive plan of pain management such as outlined by the World Health Organization, the Agency for Healthcare Research and Quality, and the American Pain Society.

2.1 Individualization of Dosage

As with any opioid drug product, adjust the dosing regimen for each patient individually, taking into account the patient’s prior analgesic treatment experience. In the selection of the initial dose of morphine sulfate, give attention to the following:

- the total daily dose, potency and specific characteristics of the opioid the patient has been taking previously;
- the reliability of the relative potency estimate used to calculate the equivalent morphine sulfate dose needed;
- the patient’s degree of opioid tolerance;
- the general condition and medical status of the patient;
- concurrent medications;
- the type and severity of the patient’s pain;
- risk factors for abuse, addiction or diversion, including a prior history of abuse, addiction or diversion.

The following dosing recommendations, therefore, can only be considered suggested approaches to what is actually a series of clinical decisions over time in the management of the pain of each individual patient.

Continual re-evaluation of the patient receiving morphine sulfate is important, with special attention to the maintenance of pain control and the relative incidence of side effects associated with therapy. During chronic therapy, especially for non-cancer-related pain, periodically re-assess the continued need for the use of opioid analgesics.

During periods of changing analgesic requirements, including initial titration, frequent contact is recommended between physician, other members of the healthcare team, the patient, and the caregiver/family.

2.2 Initiation of Therapy in Opioid-Naïve Patients

Start patients who have not been receiving opioid analgesics on morphine sulfate in the following dosing range using Oral Solution, 10 mg per 5 mL or 20 mg per 5 mL strengths:

Morphine Sulfate Oral Solution: 10 to 20 mg every 4 hours as needed for pain.

Titrate the dose based upon the individual patient’s response to their initial dose of morphine sulfate. Adjust the dose to an acceptable level of analgesia taking into account the improvement in pain intensity and the tolerability of the morphine by the patient.

The 100 mg per 5 mL (20 mg/mL) oral solution formulation is for use in opioid-tolerant patients only who have already been receiving opioid therapy. Use this strength only for patients that have already been titrated to a stable analgesic regimen using lower strengths of morphine sulfate and who can benefit from use of a smaller volume of oral solution.

2.3 Conversion to Oral Morphine Sulfate

There is inter-patient variability in the potency of opioid drugs and opioid formulations. Therefore, a conservative approach is advised when determining the total daily dose of morphine sulfate. It is better to underestimate a patient’s 24-hour oral morphine sulfate dose and make available rescue medication than to overestimate the 24-hour oral morphine sulfate dose and manage an adverse experience of overdose.

Consider the following general points regarding opioid conversions.

Conversion From Parenteral Morphine to Oral Morphine Sulfate

For conversion from parenteral to oral morphine sulfate, anywhere from 3 to 6 mg of oral morphine sulfate may be required to provide pain relief equivalent to 1 mg of parenteral morphine.

Conversion From Parenteral Oral Non-Morphine Opioids to Oral Morphine Sulfate

In converting patients from other opioids to morphine sulfate, close observation and adjustment of dosage based upon the patient’s response to morphine sulfate is imperative. Physicians and other healthcare professionals are advised to refer to published relative potency information, keeping in mind that conversion ratios are only approximate.

Conversion From Controlled-Release Oral Morphine to Oral Morphine Sulfate

For a given dose, the same total amount of morphine sulfate is available from Morphine Sulfate Oral Solution, Morphine Sulfate Tablets, and controlled-release and extended-release morphine capsules. The extended duration of release of morphine sulfate from controlled-release tablets or extended-release tablets results in reduced maximum and increased minimum plasma morphine sulfate concentrations than with shorter acting morphine sulfate products. Conversion from oral solution or immediate-release tablets to the same total daily dose of controlled-release tablets or extended-release tablets could lead to excessive sedation at peak serum levels. Therefore, dosage adjustment with close observation is necessary.

2.4 Maintenance of Therapy

Continual re-evaluation of the patient receiving morphine sulfate is important, with special attention to the maintenance of pain control and the relative incidence of side effects associated with therapy. If the level of pain increases, effort should be made to identify the source of increased pain, while adjusting the dose as described above to decrease the level of pain. During chronic therapy, especially for non-cancer-related pain (or pain associated with other terminal illnesses), periodically reassess the continued need for the use of opioid analgesics.

2.5 Cessation of Therapy

When the patient no longer requires therapy with morphine sulfate, gradually taper the dose to prevent signs and symptoms of withdrawal in the physically dependent patient.

3 DOSAGE FORMS AND STRENGTHS

For the 10 mg per 5 mL or 20 mg per 5 mL strengths: Each 5 mL of clear/blue-green Morphine Sulfate Oral Solution contains morphine sulfate USP 10 mg or 20 mg. The concentration of the 10 mg per 5 mL solution is 2 mg/mL and the concentration of the 20 mg per 5 mL solution is 4 mg/mL.

For the 100 mg per 5 mL (20 mg/mL) strength: Each 5 mL of clear/colorless or clear/pink Morphine Sulfate Oral Solution contains morphine sulfate USP 100 mg. The concentration of this solution is 20 mg/mL.

4 CONTRAINDICATIONS

Morphine sulfate is contraindicated in patients with known hypersensitivity to morphine, morphine salts, or any components of the product.

Morphine sulfate is contraindicated in patients with respiratory depression in the absence of resuscitative equipment.

Morphine sulfate is contraindicated in patients with acute or severe bronchial asthma or hypercarbia.

Morphine sulfate is contraindicated in any patient who has or is suspected of having paralytic ileus.

5 WARNINGS AND PRECAUTIONS

5.1 Risk of Medication Errors

Morphine Sulfate Oral Solution is available in 10 mg per 5 mL, 20 mg per 5 mL and 100 mg per 5 mL (20 mg/mL) concentrations. Use caution when prescribing, dispensing, and administering Morphine Sulfate Oral Solution to avoid dosing errors due to confusion between different concentrations and between mg and mL, which could result in accidental overdose and death. Use caution to ensure the dose is communicated clearly and dispensed accurately. Always use the enclosed calibrated oral syringe when administering Morphine Sulfate Oral Solution 100 mg per 5 mL (20 mg/mL) to ensure the dose is measured and administered accurately.

5.2 Respiratory Depression

Respiratory depression is the primary risk of morphine sulfate. Respiratory depression occurs more frequently in elderly or debilitated patients and in those suffering from conditions accompanied by hypoxia, hypercapnia, or upper airway obstruction, in whom even moderate therapeutic doses may significantly decrease pulmonary ventilation.

Use morphine sulfate with extreme caution in patients with chronic obstructive pulmonary disease or cor pulmonale and in patients having a substantially decreased respiratory reserve (e.g., severe kyphoscoliosis), hypoxia, hypercapnia, or pre-existing respiratory depression. In such patients, even usual therapeutic doses of morphine sulfate may increase airway resistance and decrease respiratory drive to the point of apnea. Consider alternative non-opioid analgesics, and use morphine sulfate only under careful medical supervision at the lowest effective dose in such patients.

Morphine sulfate 100 mg per 5 mL (20 mg/mL) oral solution is for use in . Administration of this formulation may cause fatal respiratory depression when administered to patients who are not tolerant to the respiratory depressant effects of opioids. opioid-tolerant patients only

5.3 Misuse, Abuse and Diversion of Opioids

Morphine sulfate is an opioid agonist and a Schedule II controlled substance. Such drugs are sought by drug abusers and people with addiction disorders. Diversion of Schedule II products is an act subject to criminal penalty.

Morphine sulfate can be abused in a manner similar to other opioid agonists, legal or illicit. This should be considered when prescribing or dispensing morphine sulfate in situations where the physician or pharmacist is concerned about an increased risk of misuse, abuse, or diversion.

Morphine sulfate may be abused by inhaling or injecting the product. These practices pose a significant risk to the abuser that could result in overdose and death. [ ] See DRUG ABUSE AND DEPENDENCE (9)

Concerns about abuse, addiction, and diversion should not prevent the proper management of pain. Healthcare professionals should contact their State Professional Licensing Board or State Controlled Substances Authority for information on how to prevent and detect abuse or diversion of this product.

5.4 Interactions with Alcohol and Drugs of Abuse

Morphine sulfate may be expected to have additive effects when used in conjunction with alcohol, other opioids, or illicit drugs that cause central nervous system depression because respiratory depression, hypotension, profound sedation, coma or death may result.

5.5 Use In Head Injury and Increased Intracranial Pressure

In the presence of head injury, intracranial lesions or a preexisting increase in intracranial pressure, the possible respiratory depressant effects of morphine sulfate and its potential to elevate cerebrospinal fluid pressure (resulting from vasodilation following CO2 retention) may be markedly exaggerated. Furthermore, morphine sulfate can produce effects on pupillary response and consciousness, which may obscure neurologic signs of further increases in intracranial pressure in patients with head injuries.

5.6 Hypotensive Effect

Morphine sulfate may cause severe hypotension in an individual whose ability to maintain blood pressure has already been compromised by a depleted blood volume or concurrent administration of drugs such as phenothiazines or general anesthetics. Morphine sulfate may produce orthostatic hypotension and syncope in ambulatory patients.

Administer morphine sulfate with caution to patients in circulatory shock, as vasodilation produced by the drug may further reduce cardiac output and blood pressure.

5.7 Gastrointestinal Effects

Do not administer morphine sulfate to patients with gastrointestinal obstruction, especially paralytic ileus because morphine sulfate diminishes propulsive peristaltic waves in the gastrointestinal tract and may prolong the obstruction.

The administration of morphine sulfate may obscure the diagnosis or clinical course in patients with acute abdominal condition.

5.8 Use in Pancreatic/Biliary Tract Disease

Use morphine sulfate with caution in patients with biliary tract disease, including acute pancreatitis, as morphine sulfate may cause spasm of the sphincter of Oddi and diminish biliary and pancreatic secretions.

5.9 Special Risk Groups

Use morphine sulfate with caution and in reduced dosages in patients with severe renal or hepatic impairment, Addison’s disease, hypothyroidism, prostatic hypertrophy, or urethral stricture, and in elderly or debilitated patients. [ ] See USE IN SPECIFIC POPULATIONS (8.5)

Exercise caution in the administration of morphine sulfate to patients with CNS depression, toxic psychosis, acute alcoholism and delirium tremens.

All opioids may aggravate convulsions in patients with convulsive disorders, and all opioids may induce or aggravate seizures in some clinical settings.

Keep Morphine Sulfate Oral Solution out of the reach of children. In case of accidental ingestion, seek emergency medical help immediately.

5.10 Driving and Operating Machinery

Caution patients that morphine sulfate could impair the mental and/or physical abilities needed to perform potentially hazardous activities such as driving a car or operating machinery.

Caution patients about the potential combined effects of morphine sulfate with other CNS depressants, including other opioids, phenothiazines, sedative/hypnotics and alcohol. [ ] See DRUG INTERACTIONS (7)

6 ADVERSE REACTIONS

Serious adverse reactions associated with morphine sulfate use include: respiratory depression, apnea, and to a lesser degree, circulatory depression, respiratory arrest, shock and cardiac arrest.

The common adverse reactions seen on initiation of therapy with morphine sulfate are dose-dependent and are typical opioid-related side effects. The most frequent of these include constipation, nausea, and somnolence. Other commonly observed adverse reactions include: lightheadedness, dizziness, sedation, vomiting, and sweating. The frequency of these events depends upon several factors including clinical setting, the patient’s level of opioid tolerance, and host factors specific to the individual. Anticipate and manage these events as part of opioid analgesia therapy.

Other less frequently observed adverse reactions expected from opioid analgesics, including morphine sulfate include:

: malaise, withdrawal syndrome Body as a Whole

: bradycardia, hypertension, hypotension, palpitations, syncope, tachycardia Cardiovascular System

: anorexia, biliary pain, dyspepsia, dysphagia, gastroenteritis, abnormal liver function tests, rectal disorder, thirst Digestive System

hypogonadism Endocrine:

: anemia, thrombocytopenia Hemic and Lymphatic System

: edema, weight loss Metabolic and Nutritional Disorders

: skeletal muscle rigidity, decreased bone mineral density Musculoskeletal

: abnormal dreams, abnormal gait, agitation, amnesia, anxiety, ataxia, confusion, convulsions, coma, delirium, depression, dry mouth, euphoria, hallucinations, lethargy, nervousness, abnormal thinking, tremor, vasodilation, vertigo, headache Nervous System

: hiccup, hypoventilation, voice alteration Respiratory System

: dry skin, urticaria, pruritus Skin and Appendages

: amblyopia, eye pain, taste perversion Special Senses

: abnormal ejaculation, dysuria, impotence, decreased libido, oliguria, urinary retention or hesitancy, anti-diuretic effect, amenorrhea Urogenital System

7 DRUG INTERACTIONS

7.1 CNS Depressants

Other central nervous system (CNS) depressants including sedatives, hypnotics, general anesthetics, antiemetics, phenothiazines, or other tranquilizers or alcohol increases the risk of respiratory depression, hypotension, profound sedation, or coma. Use morphine sulfate with caution and in reduced dosages in patients taking these agents.

7.2 Muscle Relaxants

Morphine sulfate may enhance the neuromuscular blocking action of skeletal muscle relaxants and produce an increased degree of respiratory depression.

7.3 Mixed Agonist/Antagonist Opioid Analgesics

Do not administer mixed agonist/antagonist analgesics (i.e., pentazocine, nalbuphine, and butorphanol) to patients who have received or are receiving a course of therapy with a pure opioid agonist analgesic such as morphine sulfate. In these patients, mixed agonist/antagonist analgesics may reduce the analgesic effect and/or may precipitate withdrawal symptoms.

7.4 Cimetidine

Concomitant administration of morphine sulfate and cimetidine has been reported to precipitate apnea, confusion, and muscle twitching in an isolated report. Monitor patients for increased respiratory and CNS depression when receiving cimetidine concomitantly with morphine sulfate.

7.5 Monoamine Oxidase Inhibitors (MAOIs)

MAOIs markedly potentiate the action of morphine sulfate. Allow at least 14 days after stopping treatment with MAOIs before initiating treatment with morphine sulfate.

7.6 Anticholinergics

Anticholinergics or other medications with anticholinergic activity when used concurrently with opioid analgesics may result in increased risk of urinary retention and/or severe constipation, which may lead to paralytic ileus.

7.7 P-Glycoprotein (PGP) Inhibitors

Based on published reports, PGP inhibitors (e.g. quinidine) may increase the absorption/exposure of morphine sulfate by about two fold. Therefore, exercise caution when morphine sulfate is co-administered with PGP inhibitors.

8 USE IN SPECIFIC POPULATIONS

8.1 Pregnancy

Teratogenic Effects (Pregnancy Category C)

No formal studies to assess the teratogenic effects of morphine in animals have been conducted. It is also not known whether morphine can cause fetal harm when administered to a pregnant woman or can affect reproductive capacity. Morphine should be given to a pregnant woman only if clearly needed.

In humans, the frequency of congenital anomalies has been reported to be no greater than expected among the children of 70 women who were treated with morphine during the first four months of pregnancy or in 448 women treated with this drug anytime during pregnancy. Furthermore, no malformations were observed in the infant of a woman who attempted suicide by taking an overdose of morphine and other medication during the first trimester of pregnancy.

Several literature reports indicate that morphine administered subcutaneously during the early gestational period in mice and hamsters produced neurological, soft tissue and skeletal abnormalities. With one exception, the effects that have been reported were following doses that were maternally toxic and the abnormalities noted were characteristic to those observed when maternal toxicity is present. In one study, following subcutaneous infusion of doses greater than or equal to 0.15 mg/kg to mice, exencephaly, hydronephrosis, intestinal hemorrhage, split supraoccipital, malformed sternebrae, and malformed xiphoid were noted in the absence of maternal toxicity. In the hamster, morphine sulfate given subcutaneously on gestation day 8 produced exencephaly and cranioschisis. In rats treated with subcutaneous infusions of morphine during the period of organogenesis, no teratogenicity was observed. No maternal toxicity was observed in this study, however, increased mortality and growth retardation were seen in the offspring. In two studies performed in the rabbit, no evidence of teratogenicity was reported at subcutaneous doses up to 100 mg/kg.

Nonteratogenic Effects

Controlled studies of chronic morphine exposure in pregnant women have not been conducted. Infants born to mothers who have taken opioids chronically may exhibit withdrawal symptoms, reversible reduction in brain volume, small size, decreased ventilatory response to CO and increased risk of sudden infant death syndrome. Morphine sulfate should be used by a pregnant woman only if the need for opioid analgesia clearly outweighs the potential risks to the fetus. in utero2

Published literature has reported that exposure to morphine during pregnancy is associated with reduction in growth and a host of behavioral abnormalities in the offspring. Morphine treatment during gestational periods of organogenesis in rats, hamsters, guinea pigs and rabbits resulted in the following treatment-related embryotoxicity and neonatal toxicity in one or more studies: decreased litter size, embryo-fetal viability, fetal and neonatal body weights, absolute brain and cerebellar weights, delayed motor and sexual maturation, and increased neonatal mortality, cyanosis and hypothermia. Decreased fertility in female offspring, and decreased plasma and testicular levels of luteinizing hormone and testosterone, decreased testes weights, seminiferous tubule shrinkage, germinal cell aplasia, and decreased spermatogenesis in male offspring were also observed. Decreased litter size and viability were observed in the offspring of male rats administered morphine (25 mg/kg, IP) for 1 day prior to mating. Behavioral abnormalities resulting from chronic morphine exposure of fetal animals included altered reflex and motor skill development, mild withdrawal, and altered responsiveness to morphine persisting into adulthood.

8.2 Labor and Delivery

Opioids cross the placenta and may produce respiratory depression and psycho-physiologic effects in neonates. Morphine sulfate is not recommended for use in women during and immediately prior to labor. Occasionally, opioid analgesics may prolong labor through actions which temporarily reduce the strength, duration and frequency of uterine contractions. However this effect is not consistent and may be offset by an increased rate of cervical dilatation, which tends to shorten labor. Closely observe neonates whose mothers received opioid analgesics during labor for signs of respiratory depression. Have a specific opioid antagonist, such as naloxone, available for reversal of opioid-induced respiratory depression in the neonate.

8.3 Nursing Mothers

Low levels of morphine sulfate have been detected in maternal milk. The milk:plasma morphine AUC ratio is about 2.5:1. The amount of morphine sulfate delivered to the infant depends on the plasma concentration of the mother, the amount of milk ingested by the infant, and the extent of first-pass metabolism. Because of the potential for serious adverse reactions in nursing infants from morphine sulfate including respiratory depression, sedation and possibly withdrawal symptoms, upon cessation of morphine sulfate administration to the mother, decide whether to discontinue nursing or to discontinue the drug, taking into account the importance of the drug to the mother.

8.4 Pediatric Use

The safety and effectiveness and the pharmacokinetics of Morphine Sulfate Oral Solution in pediatric patients below the age of 18 have not been established.

8.5 Geriatric Use

Elderly patients (aged 65 years or older) may have increased sensitivity to morphine sulfate. In general, use caution when selecting a dose for an elderly patient, usually starting at the low end of the dosing range, reflecting the greater frequency of decreased hepatic, renal, or cardiac function and of concomitant disease or other drug therapy.

8.6 Neonatal Withdrawal Syndrome

Chronic maternal use of opioids during pregnancy may cause newborns to suffer from neonatal withdrawal syndrome (NWS) following birth. Manifestations of this syndrome include irritability, hyperactivity, abnormal sleep pattern, high-pitched cry, tremor, vomiting, diarrhea, weight loss, and failure to gain weight. The time and amount of the mother’s last dose and the rate of elimination of the drug from the newborn may affect the onset, duration, and severity of the disorder. When severe symptoms occur, pharmacologic intervention may be required.

8.7 Gender

While evidence of greater post-operative morphine sulfate consumption in men compared to women is present in the literature, clinically significant differences in analgesic outcomes and pharmacokinetic parameters have not been consistently demonstrated. Some studies have shown an increased sensitivity to the adverse effects of morphine sulfate, including respiratory depression, in women compared to men.

8.8 Hepatic Impairment

Morphine sulfate pharmacokinetics have been reported to be significantly altered in patients with cirrhosis. Clearance was found to decrease with a corresponding increase in half-life. The M3G and M6G to morphine AUC ratios also decreased in these subjects, indicating diminished metabolic activity. Start these patients cautiously with lower doses of morphine sulfate and titrate slowly while carefully monitoring for side effects.

8.9 Renal Impairment

Morphine sulfate pharmacokinetics are altered in patients with renal failure. Clearance is decreased and the metabolites, M3G and M6G, may accumulate to much higher plasma levels in patients with renal failure as compared to patients with normal renal function. Start these patients cautiously with lower doses of morphine sulfate and titrate slowly while carefully monitoring for side effects.

9 DRUG ABUSE AND DEPENDENCE

9.1 Controlled Substance

Morphine sulfate is a mu-agonist opioid and is a Schedule II controlled substance. Morphine sulfate, like other opioids used in analgesia, can be abused and is subject to criminal diversion.

9.2 Abuse

Drug addiction is characterized by compulsive use, use for non-medical purposes, and continued use despite harm or risk of harm. Drug addiction is a treatable disease, utilizing a multi-disciplinary approach, but relapse is common. “Drug-seeking” behavior is very common in addicts and drug abusers. Drug-seeking tactics include emergency calls or visits near the end of office hours, refusal to undergo appropriate examination, testing or referral, repeated “loss” of prescriptions, tampering with prescriptions and reluctance to provide prior medical records or contact information for other treating physician(s). “Doctor shopping” to obtain additional prescriptions is common among drug abusers and people suffering from untreated addiction.

Abuse and addiction are separate and distinct from physical dependence and tolerance. Physicians should be aware that addiction may not be accompanied by concurrent tolerance and symptoms of physical dependence. The converse is also true. In addition, abuse of opioids can occur in the absence of true addiction and is characterized by misuse for non-medical purposes, often in combination with other psychoactive substances. Careful record-keeping of prescribing information, including quantity, frequency, and renewal requests is strongly advised.

Morphine sulfate is intended for oral use only. Abuse of morphine sulfate poses a risk of overdose and death. The risk is increased with concurrent abuse of alcohol and other substances. Parenteral drug abuse is commonly associated with transmission of infectious diseases such as hepatitis and HIV.

Proper assessment of the patient, proper prescribing practices, periodic re-evaluation of therapy, and proper dispensing and storage are appropriate measures that help to limit abuse of opioid drugs.

Infants born to mothers physically dependent on opioids will also be physically dependent and may exhibit respiratory difficulties and withdrawal symptoms. [ ] See USE IN SPECIFIC POPULATIONS (8.6)

9.3 Dependence

Tolerance is the need for increasing doses of opioids to maintain a defined effect such as analgesia (in the absence of disease progression or other external factors). Physical dependence is manifested by withdrawal symptoms after abrupt discontinuation of a drug or upon administration of an antagonist. Physical dependence and tolerance are not unusual during chronic opioid therapy.

The opioid abstinence or withdrawal syndrome is characterized by some or all of the following: restlessness, lacrimation, rhinorrhea, yawning, perspiration, chills, myalgia, and mydriasis. Other symptoms also may develop, including irritability, anxiety, backache, joint pain, weakness, abdominal cramps, insomnia, nausea, anorexia, vomiting, diarrhea, or increased blood pressure, respiratory rate, or heart rate.

In general, taper opioids rather than abruptly discontinue. [See ] DOSAGE AND ADMINISTRATION (2.5)

10 OVERDOSAGE

10.1 Symptoms

Acute overdosage with morphine sulfate is manifested by respiratory depression (a decrease in respiratory rate and/or tidal volume, Cheyne-Stokes respiration, cyanosis), extreme somnolence progressing to stupor or coma, skeletal muscle flaccidity, cold and clammy skin, constricted pupils, and, in some cases, pulmonary edema, bradycardia, hypotension, cardiac arrest and death.

Morphine sulfate may cause miosis, even in total darkness. Pinpoint pupils are a sign of opioid overdose but are not pathognomonic (e.g., pontine lesions of hemorrhagic or ischemic origin may produce similar findings). Marked mydriasis rather than miosis may be seen with hypoxia in overdose situations. [ ] See CLINICAL PHARMACOLOGY (12)

10.2 Treatment

Give primary attention to re-establishment of a patent airway and institution of assisted or controlled ventilation. Employ supportive measures (including oxygen and vasopressors) in the management of circulatory shock and pulmonary edema accompanying overdose as indicated. Cardiac arrest or arrhythmias may require cardiac massage or defibrillation.

Naloxone is a pure opioid antagonist that is a specific antidote to respiratory depression resulting from opioid overdose. Since the duration of reversal is expected to be less than the duration of action of morphine sulfate, carefully monitor the patient until spontaneous respiration is reliably re-established. If the response to opioid antagonists is sub-optimal or only brief in nature, administer additional antagonist as directed by the manufacturer of the product.

Do not administer opioid antagonists in the absence of clinically significant respiratory or circulatory depression secondary to morphine sulfate overdose. Administer such agents cautiously to persons who are known, or suspected to be physically dependent on morphine sulfate. In such cases, an abrupt or complete reversal of opioid effects may precipitate an acute abstinence syndrome.

In an individual physically dependent on opioids, administration of the usual dose of the antagonist will precipitate an acute withdrawal syndrome. The severity of the withdrawal symptoms experienced will depend on the degree of physical dependence and the dose of the antagonist administered. Reserve use of an opioid antagonist for cases where such treatment is clearly needed. If it is necessary to treat serious respiratory depression in the physically dependent patient, initiate administration of the antagonist with care and titrate with smaller than usual doses.

11 DESCRIPTION

Chemically, morphine sulfate is 7,8-didehydro-4,5 alpha-epoxy-17 methyl-morphinan-3,6 alpha-diol sulfate (2:1) (salt) pentahydrate with a molecular mass of 758. Morphine sulfate occurs as white, feathery, silky crystals; cubical masses of crystal; or white crystalline powder. It is soluble in water and slightly soluble in alcohol, but is practically insoluble in chloroform or ether. The octanol:water partition coefficient of morphine is 1.42 at physiologic pH and the pKa is 7.9 for the tertiary nitrogen (the majority is ionized at pH 7.4).

For the 10 mg and 20 mg per 5 mL strengths: Each 5 mL of oral solution contains 10 or 20 mg of morphine sulfate USP and the following inactive ingredients: citric acid, edetate disodium, FD&C Green No. 3 (fast green), glycerin, methylparaben (only in 20 mg/5 mL concentration), propylparaben (only in 20 mg/5 mL concentration), sodium benzoate, sorbitol and water.

For the 100 mg per 5 mL (20 mg/mL) strength: Each 5 mL of oral solution contains 100 mg of morphine sulfate USP and the following inactive ingredients: citric acid, edetate disodium, glycerin, sodium benzoate, sorbitol, and water. Additionally, the tinted solution contains D & C Red No. 33 and sucralose.

12 CLINICAL PHARMACOLOGY

12.1 Mechanism of Action

Morphine sulfate, an opioid agonist, is relatively selective for the mu receptor, although it can interact with other opioid receptors at higher doses. In addition to analgesia, the widely diverse effects of morphine sulfate include drowsiness, changes in mood, respiratory depression, decreased gastrointestinal motility, nausea, vomiting, and alterations of the endocrine and autonomic nervous system.

Effects on the Central Nervous System (CNS)

The principal therapeutic action of morphine sulfate is analgesia. Other therapeutic effects of morphine sulfate include anxiolysis, euphoria and feelings of relaxation. Although the precise mechanism of the analgesic action is unknown, specific CNS opiate receptors and endogenous compounds with morphine sulfate-like activity have been identified throughout the brain and spinal cord and are likely to play a role in the expression and perception of analgesic effects. In common with other opioids, morphine sulfate causes respiratory depression, in part by a direct effect on the brainstem respiratory centers. Morphine sulfate and related opioids depress the cough reflex by direct effect on the cough center in the medulla.

Morphine sulfate causes miosis, even in total darkness.

Effects on the Gastrointestinal Tract and on Other Smooth Muscle

Gastric, biliary and pancreatic secretions are decreased by morphine sulfate. Morphine sulfate causes a reduction in motility and is associated with an increase in tone in the antrum of the stomach and duodenum. Digestion of food in the small intestine is delayed and propulsive contractions are decreased. Propulsive peristaltic waves in the colon are decreased, while tone is increased to the point of spasm. The end result may be constipation. Morphine sulfate can cause a marked increase in biliary tract pressure as a result of spasm of the sphincter of Oddi. Morphine sulfate may also cause spasm of the sphincter of the urinary bladder.

Effects on the Cardiovascular System

In therapeutic doses, morphine sulfate does not usually exert major effects on the cardiovascular system. Morphine sulfate produces peripheral vasodilation which may result in orthostatic hypotension and fainting. Release of histamine can occur, which may play a role in opioid-induced hypotension. Manifestations of histamine release and/or peripheral vasodilation may include pruritus, flushing, red eyes and sweating.

Endocrine System

Opioid agonists have been shown to have a variety of effects on the secretion of hormones. Opioids inhibit the secretion of ACTH, cortisol, and luteinizing hormone (LH) in humans. They also stimulate prolactin, growth hormone (GH) secretion, and pancreatic secretion of insulin and glucagon in humans and other species, rats and dogs. Thyroid stimulating hormone (TSH) has been shown to be both inhibited and stimulated by opioids.

Immune System

Opioids have been shown to have a variety of effects on components of the immune system in and animal models. The clinical significance of these findings is unknown. in vitro

12.2 Pharmacodynamics

Morphine sulfate concentrations are not predictive of analgesic response, especially in patients previously treated with opioids. The minimum effective concentration varies widely and is influenced by a variety of factors, including the extent of previous opioid use, age and general medical condition. Effective doses in tolerant patients may be significantly higher than in opioid-naïve patients.

12.3 Pharmacokinetics

Absorption

Morphine sulfate is about two-thirds absorbed from the gastrointestinal tract with the maximum analgesic effect occurring 60 minutes post-administration. The oral bioavailability of morphine sulfate is less than 40% and shows large inter-individual variability due to extensive pre-systemic metabolism.

Food Effects

Although the presence of a food effect was not assessed with morphine sulfate oral solution, significant food effect is not expected with a solution formulation.

Steady-State

Administration of the 30 mg Morphine Sulfate Tablet and 30 mg of Morphine Sulfate Oral Solution every six hours for 5 days resulted in a comparable 24-hour exposure (AUC). The steady-state levels were achieved within 48 hours for both tablets and solution. The mean steady state Cmax values were about 78 and 58 ng/mL for tablet and solution, respectively.

Distribution

Once absorbed, morphine sulfate is distributed to skeletal muscle, kidneys, liver, intestinal tract, lungs, spleen and brain. Although the primary site of action is the CNS, only small quantities cross the blood-brain barrier. Morphine sulfate also crosses the placental membranes and has been found in breast milk. The volume of distribution of morphine sulfate is approximately 1 to 6 L/kg, and morphine sulfate is 20 to 35% reversibly bound to plasma proteins.

Metabolism

The major pathway of morphine sulfate detoxification is conjugation, either with D-glucuronic acid to produce glucuronides or with sulfuric acid to produce morphine-3-etheral sulfate. While a small fraction (less than 5%) of morphine sulfate is demethylated, virtually all morphine sulfate is converted by hepatic metabolism to the 3- and 6-glucuronide metabolites (M3G and M6G; about 50% and 15%, respectively). M6G has been shown to have analgesic activity but crosses the blood-brain barrier poorly, while M3G has no significant analgesic activity.

Excretion

Most of a dose of morphine sulfate is excreted in urine as M3G and M6G, with elimination of morphine sulfate occurring primarily as renal excretion of M3G. Approximately 10% of the dose is excreted unchanged in urine. A small amount of glucuronide conjugates are excreted in bile, with minor enterohepatic recycling. Seven to 10% of administered morphine sulfate is excreted in the feces.

The mean adult plasma clearance is approximately 20 to 30 mL/min/kg. The effective terminal half-life of morphine sulfate after IV administration is reported to be approximately 2 hours. In some studies involving longer periods of plasma sampling, a longer terminal half-life of morphine sulfate of about 15 hours was reported.

Race

There may be some pharmacokinetic differences associated with race. In one published study, Chinese subjects given intravenous morphine sulfate had a higher clearance when compared to Caucasian subjects (1852 +/- 116 mL/min compared to 1495 +/- 80 mL/min).

13 NONCLINICAL TOXICOLOGY

13.1 Carcinogenesis, Mutagenesis, Impairment of Fertility

Carcinogenesis

Studies in animals to evaluate the carcinogenic potential of morphine sulfate have not been conducted.

Mutagenesis

No formal studies to assess the mutagenic potential of morphine have been conducted. In the published literature, morphine was found to be mutagenic increasing DNA fragmentation in human T-cells. Morphine was reported to be mutagenic in the mouse micronucleus assay and positive for the induction of chromosomal aberrations in mouse spermatids and murine lymphocytes. Mechanistic studies suggest that the clastogenic effects reported with morphine in mice may be related to increases in glucocorticoid levels produced by morphine in this species. In contrast to the above positive findings, studies in the literature have also shown that morphine did not induce chromosomal aberrations in human leukocytes or translocations or lethal mutations in . in vitroin vivoin vivoin vitro Drosophila

Impairment of Fertility

No formal nonclinical studies to assess the potential of morphine to impair fertility have been conducted. Several nonclinical studies from the literature have demonstrated adverse effects on male fertility in the rat from exposure to morphine. One study in which male rats were administered morphine sulfate subcutaneously prior to mating (up to 30 mg/kg twice daily) and during mating (20 mg/kg twice daily) with untreated females, a number of adverse reproductive effects including reduction in total pregnancies, higher incidence of pseudopregnancies, and reduction in implantation sites were seen. Studies from the literature have also reported changes in hormonal levels (i.e. testosterone, luteinizing hormone, serum corticosterone) following treatment with morphine. These changes may be associated with the reported effects on fertility in the rat.

16 HOW SUPPLIED/STORAGE AND HANDLING

NDC:17856-0237-5 in a CUP of 5 SOLUTIONS

17 PATIENT COUNSELING INFORMATION

See Medication Guide

Provide the following information to patients receiving morphine sulfate or their caregivers:

- Advise patients that morphine sulfate is a narcotic pain reliever, and should be taken only as directed.
- Advise patients that Morphine Sulfate Oral Solution is available in three concentrations: 10 mg per 5 mL, 20 mg per 5 mL and 100 mg per 5 mL (20 mg/mL). Carefully instruct patients about which concentration they have been prescribed and how to measure and take the correct dose of Morphine Sulfate Oral Solution. Advise patients whenever the prescribed concentration is changed to avoid dosing errors which could result in accidental overdose and death.
- Advise patients to always use the enclosed calibrated oral syringe when administering Morphine Oral Solution 100 mg per 5 mL (20 mg/mL) to ensure the dose is measured and administered accurately.
- The 100 mg per 5 mL (20 mg/mL) formulation is only for patients who are already receiving opioid-therapy and have demonstrated opioid-tolerance. Use of this formulation may cause fatal respiratory depression when administered to patients who have not had previous exposure to opioids.
- Advise patients not to adjust the dose of morphine sulfate without consulting with a physician or other healthcare professional.
- Advise patients that morphine sulfate may cause drowsiness, dizziness, or lightheadedness and may impair mental and/or physical ability required for the performance of potentially hazardous tasks (e.g., driving, operating machinery). Advise patients started on morphine sulfate or patients whose dose has been adjusted to refrain from any potentially dangerous activity until it is established that they are not adversely affected.
- Instruct patients not to combine morphine sulfate with central nervous system depressants (such as sleep aids, tranquilizers, antihistamines, general anesthetics, phenothiazines, other opioids, and monoamine oxidase [MAO] inhibitors) except by the orders of the prescribing physician, and not to combine with alcohol because dangerous additive effects may occur, resulting in serious injury or death.
- Instruct women of childbearing potential who become or are planning to become pregnant to consult a physician prior to initiating or continuing therapy with morphine sulfate.
- Advise patients that safe use in pregnancy has not been established and that prolonged use of opioid analgesics during pregnancy may cause fetal-neonatal physical dependence, Neonatal withdrawal may also occur.
- If patients have been receiving treatment with morphine sulfate for more than a few weeks and cessation of therapy is indicated, counsel them on the importance of safely tapering the dose as abrupt discontinuation of the medication could precipitate withdrawal symptoms. Provide a dose schedule to accomplish a gradual discontinuation of the medication.
- Advise patients that morphine sulfate is a potential drug of abuse. They must protect it from theft. It should never be given to anyone other than the individual for whom it was prescribed.
- Instruct patients to keep morphine sulfate in a secure place out of the reach of children. When morphine sulfate is no longer needed, the unused oral solution should be destroyed by flushing down the toilet.
- Advise patients taking morphine sulfate of the potential for severe constipation; appropriate laxatives and/or stool softeners as well as other appropriate treatments should be initiated from the onset of opioid therapy.
- Advise patients of the most common adverse events that may occur while taking morphine sulfate: constipation, nausea, somnolence, lightheadedness, dizziness, sedation, vomiting, and sweating.

Roxane Laboratories, Inc.

Columbus, Ohio 43216

10008802/02 Revised February 2015

©RLI, 2015

Medication Guide

MORPHINE SULFATE (mor-pheen) (CII)

Oral Solution

BOXED WARNING

. IMPORTANT: Keep Morphine Sulfate Oral Solution in a safe place away from children. Accidental use by a child is a medical emergency and can cause death. If a child accidentally takes Morphine Sulfate Oral Solution, get emergency help right away

Read the Medication Guide that comes with Morphine Sulfate Oral Solution before you start taking it and each time you get a new prescription. There may be new information. This Medication Guide does not take the place of talking with your healthcare provider about your medical condition or your treatment.

What is the most important information I should know about Morphine Sulfate Oral Solution?

Morphine Sulfate Oral Solution can cause serious side effects, including death.

•Take Morphine Sulfate Oral Solution exactly as prescribed by your healthcare provider. If you take the wrong dose or strength of Morphine Sulfate Oral Solution, you could overdose and die.•It is especially important when you take Morphine Sulfate Oral Solution that you know exactly what dose and strength to take, and the right way to measure your medicine. Your healthcare provider or pharmacist should show you the right way to measure your medicine.•Always use the oral syringe provided with Morphine Sulfate Oral Solution, 100 mg per 5 mL (20 mg/mL) to help make sure you measure the right amount.•The oral solution comes in several different doses (amount of medicine per mL) and strengths (number of mgs).•Do not take the strongest dose of Morphine Sulfate Oral Solution, 100 mg per 5 mL (20 mg/mL), unless you are “opioid tolerant.” Opioid tolerant means that you have been regularly using Morphine Sulfate Oral Solution or another opioid medicine for your constant (around the clock) pain and your body is used to it.

What is Morphine Sulfate Oral Solution?

Morphine Sulfate Oral Solution is in a group of drugs called narcotic pain relievers. Morphine Sulfate Oral Solution is only for adults who have moderate to severe pain.

•Morphine Sulfate Oral Solution is a prescription medicine that is used to manage moderate to severe pain that is expected to last a short period of time (acute), and pain that continues around-the-clock and is expected to last for a long period of time (chronic).•Morphine Sulfate Oral Solution is a federally controlled substance (CII) because it is a strong opioid pain medicine that can be abused by people who abuse prescription medicines or street drugs.•Prevent theft, misuse or abuse. Keep Morphine Sulfate Oral Solution in a safe place to keep it from being stolen. Morphine Sulfate Oral Solution can be a target for people who misuse or abuse prescription medicines or street drugs.•Never give Morphine Sulfate Oral Solution to anyone else, even if they have the same symptoms you have. It may harm them or even cause death.•Selling or giving away this medicine is against the law.•It is not known if Morphine Sulfate Oral Solution is safe and effective in children under age 18 years of age.•Morphine Sulfate Oral Solution 100 mg per 5 mL (20 mg/mL) is only for adults with moderate to severe pain who are already using an opioid narcotic pain medicine and have been using this medicine continuously for several weeks or longer.

Who should not take Morphine Sulfate Oral Solution?

•Do not take Morphine Sulfate Oral Solution if you:•See the end of this Medication guide for a complete list of ingredients in Morphine Sulfate Oral Solution. are allergic to morphine, morphine salts or any of the ingredients in Morphine Sulfate Oral Solution.•are having an asthma attack or have severe asthma, trouble breathing, or lung problems•have a bowel blockage called paralytic ileus

What should I tell my healthcare provider before taking Morphine Sulfate Oral Solution?

•Before taking Morphine Sulfate Oral Solution, tell your healthcare provider if you:•have trouble breathing or lung problems•have had a head injury•have liver or kidney problems•have had adrenal gland problems, such as Addison’s disease•have severe scoliosis that affects your breathing•have thyroid problems•have problems urinating or enlargement of your prostate•have had convulsions or seizures•have a past or present drinking problem or alcoholism•have severe mental problems or hallucinations (seeing or hearing things that are not really there).•have constipation or other bowel problems•have problems with your pancreas or gallbladder•have past or present substance abuse or drug addiction•plan to have surgery•have any other medical conditions•are pregnant or plan to become pregnant. It is not known if Morphine Sulfate Oral Solution will harm your unborn baby. Talk to your healthcare provider if you are pregnant or plan to become pregnant.

If you take Morphine Sulfate Oral Solution regularly before your baby is born, your newborn baby may have withdrawal symptoms because their body has become used to the medicine. Symptoms of withdrawal in a newborn baby may include:

•irritability•being very active•problems sleeping•high pitched cry•shaking (tremors)•vomiting•diarrhea or more stools than normal•weight loss•fever

If you take Morphine Sulfate right before your baby is born, your baby could have breathing problems.

•are breast-feeding or plan to breast-feed. Some Morphine Sulfate passes into your breast milk. A nursing baby could become very sleepy and have problems breathing or feeding well. If you stop breast-feeding, your baby may have withdrawal symptoms. See the list of withdrawal symptoms above. You and your healthcare provider should decide if you will take Morphine Sulfate Oral Solution or breast-feed.

, including prescription and non-prescription medicines, vitamins, and herbal supplements. Sometimes the doses of medicines that you take with Morphine Sulfate Oral Solution may need to be changed if used together. Be especially careful about taking other medicines that make you sleepy such as: Tell your healthcare provider about all the medicines you take

•sleeping pills•other pain medicines•anti-nausea medicines•tranquilizers•muscle relaxants•antihistamines•anti-anxiety medicines•anti-depressants•anticholinergic medicines•antibiotic or antifungal medicines•heart medicines•anti-seizure medicines•Tell your healthcare provider if you take cimetidine (Tagamet).•Do not take Morphine Sulfate Oral Solution if you already take a monoamine oxidase inhibitor medicine (MAOI) or within 14 days after you stop taking an MAOI medicine.•Do not take any new medicine while using Morphine Sulfate Oral Solution until you have talked with your healthcare provider or pharmacist. They will tell you if it is safe to take other medicines with Morphine Sulfate Oral Solution.

Ask your healthcare provider if you are not sure if your medicine is one listed above.

Know the medicines you take. Keep a list of them and show it to your healthcare provider and pharmacist when you get a new medicine.

How should I take Morphine Sulfate Oral Solution?

•See “What is the most important information I should know about Morphine Sulfate Oral Solution?”•. Do not change your dose unless your healthcare provider tells you to. Your healthcare provider may change your dose after seeing how the medicine affects you. Call your healthcare provider if your pain is not well controlled with your prescribed dose of Morphine Sulfate Oral Solution. Take Morphine Sulfate Oral Solution exactly as prescribed•. You can take Morphine Sulfate Oral Solution with or without food•. Always use the oral syringe provided with your Morphine Sulfate Oral Solution, 100 mg per 5 mL (20 mg/mL) to help make sure you measure the right amount. See the Instructions for Use at the end of this Medication Guide for information about how to measure your dose the right way. Ask your healthcare provider or pharmacist if you are not sure what dose of Morphine Sulfate Oral Solution you should take or if you are not sure how to use the oral syringe. Make sure you understand exactly how to measure your dose•If you have been taking Morphine Sulfate Oral Solution for more than a few weeks, stopping Morphine Sulfate Oral Solution suddenly can make you sick with withdrawal symptoms (for example, nausea, vomiting, diarrhea, anxiety, and shivering). If your healthcare provider decides you no longer need Morphine Sulfate Oral Solution, ask how to slowly reduce this medicine. Do not stop taking Morphine Sulfate Oral Solution without talking to your healthcare provider. Do not stop taking Morphine Sulfate Oral Solution suddenly.•you can take the dose when you remember it if you have pain, or you can wait for the next dose. If you miss one dose of Morphine Sulfate Oral Solution

Talk with your healthcare provider regularly about your pain to see if you still need to take Morphine Sulfate Oral Solution.

What should I avoid while taking Morphine Sulfate Oral Solution?

•You should not drink alcohol while using Morphine Sulfate Oral Solution. Drinking alcohol with Morphine Sulfate Oral Solution may increase your risk of having dangerous side effects or death.•especially when you start taking Morphine Sulfate Oral Solution and when your dose is changed, until you know how Morphine Sulfate Oral Solution affects you. Morphine Sulfate Oral Solution can make you sleepy. Ask your healthcare provider to tell you when it is okay to do these activities. Do not drive, operate heavy machinery, or do other dangerous activities,

What are the possible side effects of Morphine Sulfate Oral Solution?

•See “What is the most important information I should know about Morphine Sulfate Oral Solution?”•Morphine Sulfate Oral Solution can cause serious breathing problems that can become life-threatening, especially if Morphine Sulfate Oral Solution is used the wrong way. Call your healthcare provider or get help right away if:•your breathing slows down•you have shallow breathing (little chest movement with breathing)•you feel faint, dizzy, confused, or•you have any other unusual symptoms

These can be symptoms that you have taken too much Morphine Sulfate Oral Solution (overdose) or the dose is too high for you. These symptoms may lead to serious problems or death if not treated right away.

•This can make you feel dizzy if you get up too fast from sitting or lying down. Low blood pressure is also more likely to happen if you take other medicines that can also lower your blood pressure. Severe low blood pressure can happen if you lose blood or take certain other medicines. Morphine Sulfate Oral Solution can cause your blood pressure to drop.•The chance is higher if you are or have been addicted to or abused other medicines, street drugs, or alcohol, or if you have a history of mental problems. There is a risk of abuse or addiction with Morphine Sulfate Oral Solution.•Do not stop taking Morphine Sulfate or any other opioid without talking to your healthcare provider about how to slowly stop your medicine. You could become sick with uncomfortable withdrawal symptoms because your body has become used to these medicines. Physical dependence is not the same as drug addiction. Tell your healthcare provider if you have any of these symptoms of withdrawal while slowly stopping Morphine Sulfate Oral Solution: Morphine Sulfate can cause physical dependence.•feel restless•tearing eyes•runny nose•yawning•sweating•chills or hair on your arms “stand up”•muscle aches, backache•dilated pupils of your eyes•feel irritable or anxious•trouble sleeping•nausea, loss of appetite, vomiting, diarrhea, stomach-area (abdominal) cramps•increase in your blood pressure•faster breathing, or faster heart beats

•Common side effects of Morphine Sulfate Oral Solution include:•constipation•nausea•sleepiness•lightheadedness•dizziness•drowsiness•vomiting•sweating

Constipation (not often enough or hard bowel movements) is a very common side effect of pain medicines (opioids). Talk to your healthcare provider about dietary changes, and the use of laxatives (medicines to treat constipation) and stool softeners to prevent or treat constipation while taking Morphine Sulfate Oral Solution.

Tell your healthcare provider if you have any side effect that bothers you or that does not go away.

These are not all the possible side effects of Morphine Sulfate Oral Solution. For more information, ask your healthcare provider or pharmacist.

Call your doctor for medical advice about side effects. You may report side effects to FDA at 1-800-FDA-1088.

How should I store Morphine Sulfate Oral Solution?

•Store Morphine Sulfate Oral Solution at 68º to 77º F (20º to 25º C).•After you stop taking Morphine Sulfate Oral Solution, flush the unused oral solution down the toilet.•Keep Morphine Sulfate out of the reach of children. Accidental overdose by a child is a medical emergency and can lead to death.

General information about Morphine Sulfate Oral Solution

Medicines are sometimes prescribed for purposes other than those listed in a Medication Guide. Do not use Morphine Sulfate Oral Solution for a condition for which it was not prescribed. Do not give your Morphine Sulfate Oral Solution to other people, even if they have the same symptoms you have. Selling or giving away Morphine Sulfate Oral Solution may harm others, may cause death, and is against the law.

This Medication Guide summarizes the most important information about Morphine Sulfate Oral Solution. If you would like more information, talk with your healthcare provider. You can ask your healthcare provider or pharmacist for information about Morphine Sulfate Oral Solution that is written for healthcare professionals.

For more information about Morphine Sulfate Oral Solution, go to or call Roxane Laboratories, Inc. at 1-800-962-8364. www.roxane.com

What are the ingredients in Morphine Sulfate Oral Solution?

morphine sulfate USP Active ingredient:

citric acid, edetate disodium, glycerin, sodium benzoate, sorbitol, and water. Inactive ingredients:

•The 10 mg/5 mL oral solution also contains: FD&C Green No. 3 (fast green)•The 20 mg/5 mL oral solution also contains: FD&C Green No. 3 (fast green), methylparaben, and propylparaben•The 100 mg per 5 mL tinted solution also contains D & C Red No. 33 and sucralose.

This Medication Guide has been approved by the U.S. Food and Drug Administration.

Roxane Laboratories, Inc.

Columbus, Ohio 43216

10008802/02 Revised February 2015

©RLI, 2015

INSTRUCTIONS FOR USE

MORPHINE SULFATE ORAL SOLUTION 100 mg per 5 mL (20 mg/mL)

Oral Syringe

Important information about measuring Morphine Sulfate Oral Solution

• Always use the oral syringe provided with your Morphine Sulfate Oral Solution to make sure you measure the right amount.

• Measure the dose of medicine from the widest part of the plunger. Do not measure from the narrow tip. See figure 1

1. Insert the tip of the oral syringe into the medicine bottle.

2. Pull back the plunger to the line that matches the dose prescribed by your healthcare provider.

3. Remove the oral syringe from the medicine bottle.

4. Take your medicine by slowly pushing the plunger until the oral syringe is empty.